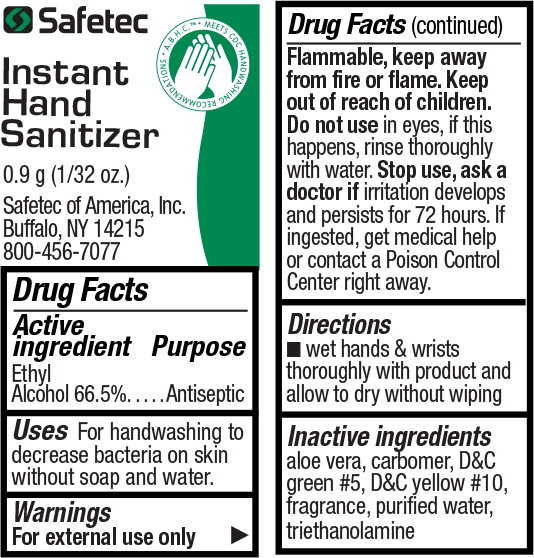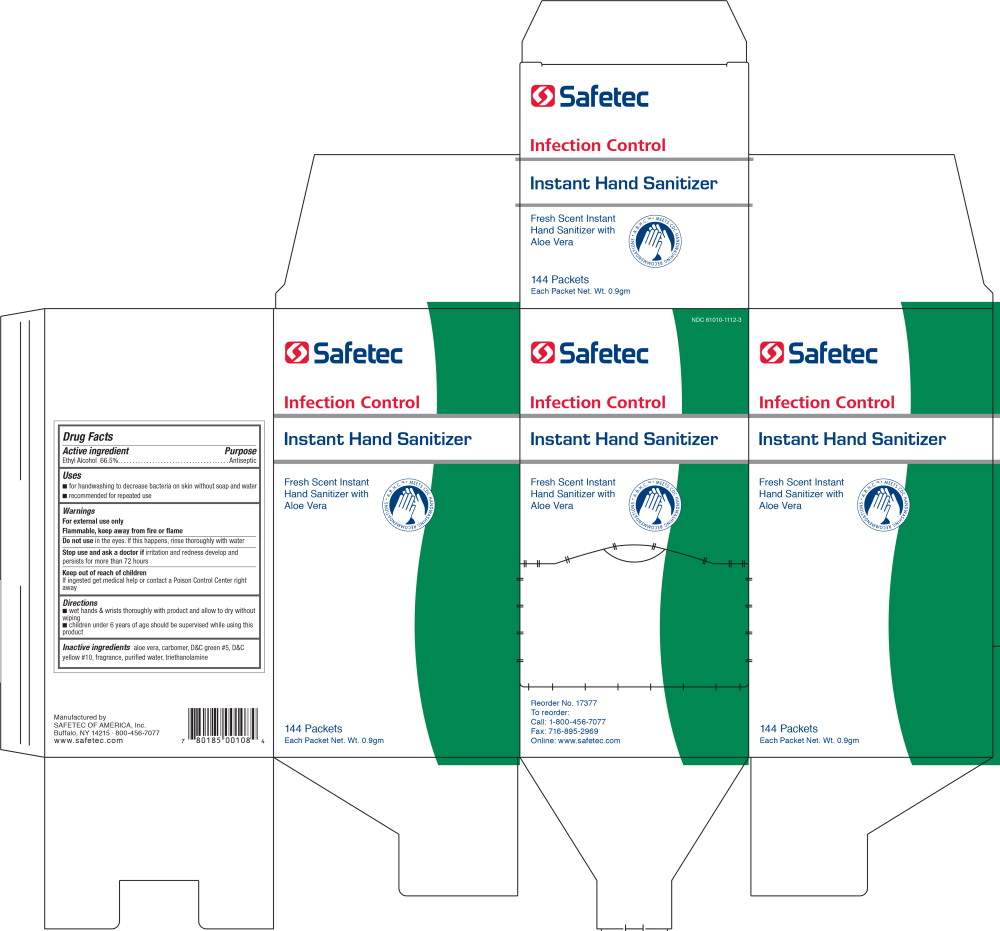 DRUG LABEL: Instant Hand Sanitizer
NDC: 61010-1112 | Form: GEL
Manufacturer: Safetec of America
Category: otc | Type: HUMAN OTC DRUG LABEL
Date: 20260116

ACTIVE INGREDIENTS: ALCOHOL
 665 mL/1 L
INACTIVE INGREDIENTS: ALOE; WATER; TROLAMINE

61010-1112-2,-3,-8, Instant Hand Sanitzer

Active ingredient

Ethyl Alcohol 66.5%

Purpose

Antiseptic

Uses

- For handwashing to decrease bacteria on skin without soap and water

Warnings

For external use only

Flammable, keep away from fire or flame.

Keep out of reach of children.

DO NOT USE

Do not usein eyes, if this happens, rinse thoroughly with water.

Stop use, ask a doctor ifirritation develops and persists for 72 hours. If ingested, get medical help or contact a Poison Control Center right away.

Directions

- wet hands & wrists thoroughly with product and allow to dry without wiping

Inactive ingredients

aloe vera, carbomer, D&C green #5, D&C yellow #10, fragrance, purified water, triethanolamine

PRINCIPAL DISPLAY PANEL – 0.9g Pouch Label

Safetec

A.B.H.C. ™ MEETS CDC HANDWASHING RECOMMENDATIONS

Instant
Hand
Sanitizer

0.9 g (1/32 oz.)

Safetec of America, Inc.

Buffalo, NY 14215

800-456-7077

PRINCIPAL DISPLAY PANEL – 144 Packets Box Label

NDC 61010-1112-3

Safetec

Infection Control

Instant Hand Sanitizer

Fresh Scent Instant
Hand Sanitizer with
Aloe Vera

A.B.H.C. ™ MEETS CDC HANDWASHING RECOMMENDATIONS

144 Packets

Each Packet Net. Wt. 0.9g